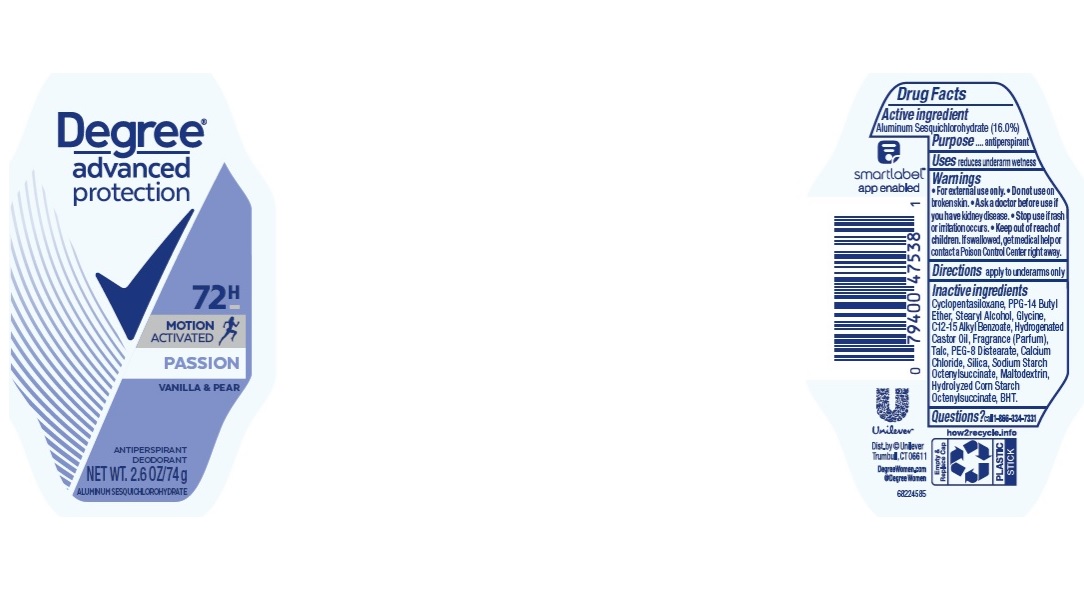 DRUG LABEL: Degree
NDC: 64942-1713 | Form: STICK
Manufacturer: Conopco Inc. d/b/a/ Unilever
Category: otc | Type: HUMAN OTC DRUG LABEL
Date: 20241110

ACTIVE INGREDIENTS: ALUMINUM SESQUICHLOROHYDRATE 16 g/100 g
INACTIVE INGREDIENTS: TALC; CYCLOMETHICONE 5; HYDROGENATED CASTOR OIL; BUTYLATED HYDROXYTOLUENE; PPG-14 BUTYL ETHER; STEARYL ALCOHOL; CALCIUM CHLORIDE; SILICON DIOXIDE; ALKYL (C12-15) BENZOATE; PEG-8 DISTEARATE; GLYCINE; MALTODEXTRIN

Degree Advanced Protection 72H Motion Activated Passion Vanilla & Pear Antiperspirant Deodorant

DEGREE ADVANCED PROTECTION 72H MOTION ACTIVATED PASSION VANILLA & PEAR ANTIPERSPIRANT DEODORANT - Aluminum Sesquichlorohydrate stick

Degree Advanced Protection 72H Motion Activated Passion Vanilla & Pear Antiperspirant Deodorant

Drug Facts

Active ingredient

Aluminum Sesquichlorohydrate (16.0 %)

Purpose

antiperspirant

Uses

• reduces underarm wetness

Warnings

• For external use only.
• Do not use on broken skin .
• Ask a doctor before use if you have kidney disease.
• Stop use if rash or irritation occurs.

• Keep out of reach of children.

If swallowed, get medical help or contact a Poison Control Center right away.

Directions

apply to underarms only

Inactive ingredients

Cyclopentasiloxane, PPG-14 Butyl Ether, Stearyl Alcohol, Glycine, C12-15 Alkyl Benzoate, Hydrogenated Castor Oil, Fragrance (Parfum), Talc, PEG-8 Distearate, Calcium Chloride, Silica, Sodium Starch Octenylsuccinate, Maltodextrin, Hydrolyzed Corn Starch Octenylsuccinate, BHT.

Questions?

Call toll-free 1-866-334-7331